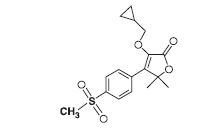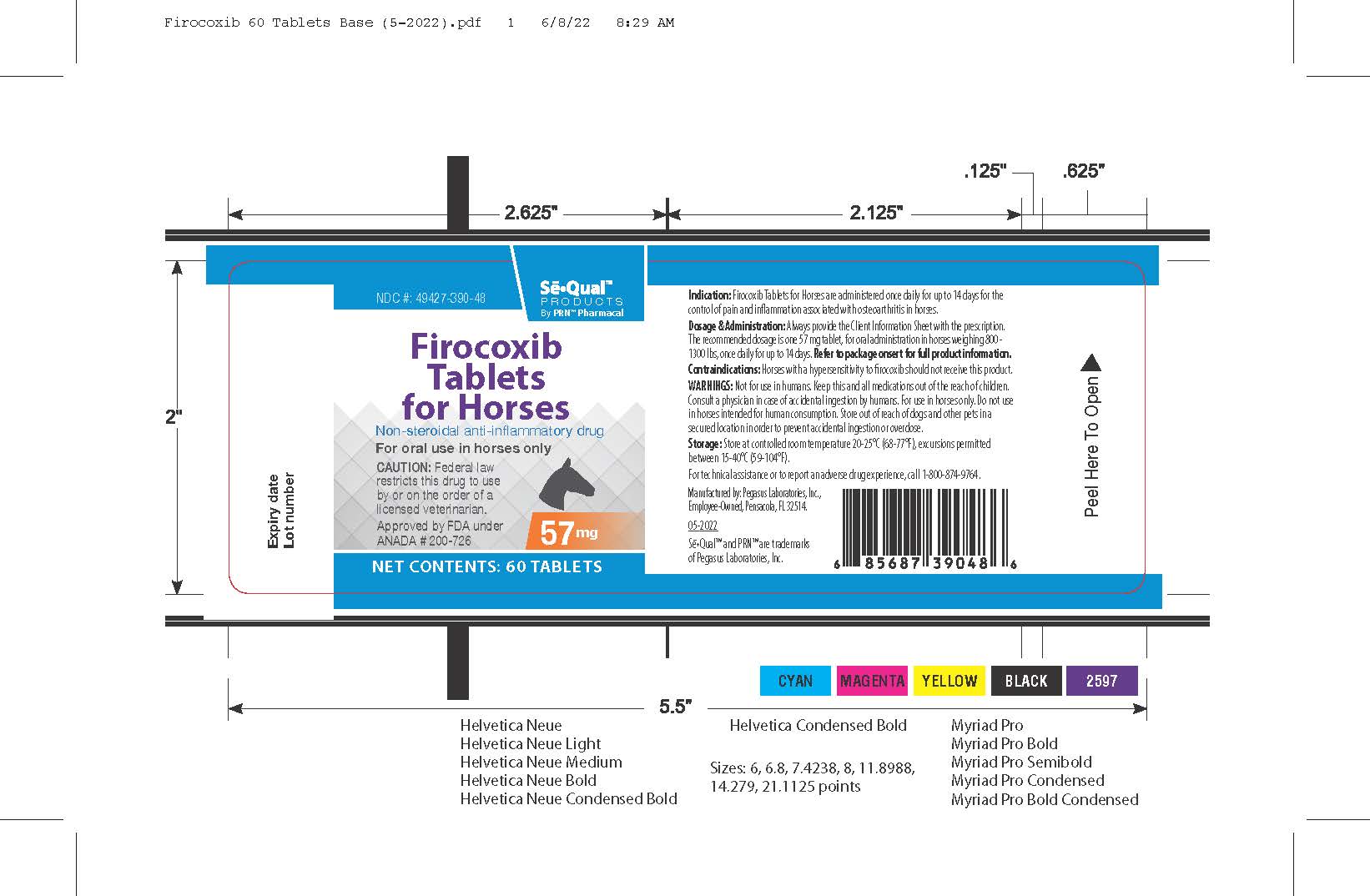 DRUG LABEL: Firocoxib for Horses
NDC: 49427-390 | Form: TABLET
Manufacturer: Pegasus Laboratories, Inc.
Category: animal | Type: PRESCRIPTION ANIMAL DRUG LABEL
Date: 20251229

ACTIVE INGREDIENTS: FIROCOXIB 57 mg/1 1

Firocoxib Tablets for Horses

Firocoxib Tablets for Horses 57 mg

For oral use in horses only

CAUTION:

Federal law restricts this drug to use by or on the order of a licensed veterinarian.

Description:

Firocoxib Tablets for Horses belongs to the coxib class of non-narcotic, non-steroidal anti-inflammatory drugs (NSAIDs). Firocoxib is a white crystalline compound described chemically as 3 (cyclopropylmethoxy)-4-(4-methylsulfonyl)phenyl)-5,5-dimethylfuranone. The empirical formula is C17H20O5S, and the moleclar weight in 336.4 g/mol. The structural formula is shown below:

Indications:

Firocoxib Tablets for Horses are administered once daily for up to 14 days for the control of pain and inflmmation associated with osteoarthrtis in horses.

Dosage and Administration:

Always provide the Client Information Sheet with the prescription. The recommended dosage of Firocoxib Tablets for Horses is one 57 mg tablet administered orally to horses weiging 800 - 1300 lbs, once daily for up to 14 days. For ease of administration, Firocoxib Tablets for Horses may be given with food.

The overall duration of treatment with any firocoxib formulation in horses, including tablets, injection or oral paste should not exceed 14 days. Please see the package insert for firocoxib injection or oral paste for appropriate prescribing information for those formulations.

Contraindications:

Horses with a hypersensitivity to firocoxib should not receive Firocoxib Tablets for Horses.

Warnings:

For use in horses only. Do not use in horses intended for human consumption. Store Firocoxib Tablets for Horses out of the reach of dogs and other pets in a secured location in order to prevent accidental ingestion or overdose.

Human Warnings: Not for use in humans. Keep this and all medications out of the reach of children. Consult a physician in case of accidental ingestion by humans.

Precautions:

Horses should undergo a thorough history and physical examination before initiation of NSAID therapy. Appropriate laboratory tests should be conducted to establish hematological and serum biochemical baseline data before and periodically during administration of any NSAID. Clients should be advised to observe for signs of potential drug toxicity and be given a Client Information Sheet with each prescription. See Information for Owner or Person Treating Horse section of this package insert.

Treatment with Firocoxib Tablets for Horses should be terminated if signs such as inappetence, colic, abnormal feces, or lethargy are observed.

As a class, cyclooxygenase inhibitory NSAIDs may be associated with gastrointestinal, renal, and hepatic toxicity. Sensitivity to drug-associated adverse events varies with the individual patient. Horses that have experienced adverse reactions from one NSAID may experience adverse reactions from another NSAID. Patients at greatest risk for adverse events are those that are dehydrated, on diuretic therapy, or those with existing renal, cardiovascular, and/or hepatic dysfunction. Concurrent administration of potentially nephrotoxic drugs should be carefully approached or avoided. NSAIDs may inhibit the prostaglandins that maintain normal homeostatic function. Such anti-prostaglandin effects may result in clinically significant disease in patients with underlying or pre-existing disease that has not been previously diagnosed. Since many NSAIDs possess the potential to produce gastrointestinal ulcerations and/or gastrointestinal perforation, concomitant use of Firocoxib Tablets for Horses with other anti-inflammatory drugs, such as NSAIDs or corticosteroids, should be avoided.

The concomitant use of protein bound drugs with Firocoxib Tablets for Horses has not been studied in horses. The influence of concomitant drugs that may inhibit the metabolism of Firocoxib Tablets for Horses has not been evaluated. Drug compatibility should be monitored in patients requiring adjunctive therapy.

The safe use of Firocoxib Tablets for Horses in horses less than one year in age, horses used for breeding, or in pregnant or lactating mares has not been evaluated.

Consider appropriate washout times when switching from one NSAID to another NSAID or corticosteroid.

Adverse Reactions:

The safety and effectiveness of firocoxib tablets was established in a relative bioavailability study comparing firocoxib tablets and firocoxib oral paste. Therefore, additional field studies were not performed to support the effectiveness of firocoxib tablets.

In controlled field studies, 127 horses (ages 3 to 37 years) were evaluated for safety when given firocoxib oral paste at a dose of 0.045 mg/lb (0.1 mg/kg) orally once daily for up to 14 days. The following adverse reactions were observed. Horses may have experienced more than one of the observed adverse reactions during the study.

Table 1: Adverse Reactions Seen in U.S. Field Studies with firocoxib oral paste:
Adverse; Reactions | Firocoxib; n = 127 | Active control; n = 125
Abdominal Pain | 0 | 1
Diarrhea | 2 | 0
Excitation | 1 | 0
Lethargy | 0 | 1
Loose stool | 1 | 0
Polydipsia | 0 | 1
Uticaria | 0 | 1

In these field trials, firocoxib oral paste was safely used concomitantly with other therapies, including vaccines, anthelmintics, and antibiotics. The safety data sheet (SDS) contains more detailed occupational safety information.

To report suspected adverse events, for technical assistance, or to obtain a copy of the SDS, contact Pegasus Laboratories at 1-800-874-9764. For additional information about adverse drug experience reporting for animal drugs, contact FDA at 1-888-FDA-VETS or online at http://www.fda.gov/reportanimalae.

Information for Owner or Person Treating Horse:

A Client Information Sheet should be provided to the person treating the horse. Treatment administrators and caretakers should be aware of the potential for adverse reactions and the clinical signs associated with NSAID intolerance. Adverse reactions may include erosions and ulcers of the gums, tongue, lips and face, weight loss, colic, diarrhea, or icterus. Serious adverse reactions associated with this drug class can occur without warning and, in some situations, result in death. Clients should be advised to discontinue NSAID therapy and contact their veterinarian immediately if any of these signs of intolerance are observed. The majority of patients with drug-related adverse reactions recover when the signs are recognized, drug administration is stopped, and veterinary care is initiated.

Clinical Pharmacology:

Relative Bioavailability Study A pharmacokinetic study was conducted to compare the relative bioavailability of an oral firocoxib tablet containing 57 mg firocoxib to the approved paste formulation. The criteria for the Test/Reference (T/R) ratios and the 90% Confidence Intervals (CI) of firocoxib tablets (test product) were adjusted on the basis of the safety and effectiveness data for the oral paste (reference product). The lower bound of the 90% CI for effectiveness was defined by the minimal effective plasma concentration in the study used to support the dosage characterization of firocoxib oral paste. Effectiveness was based upon the area under the plasma drug concentration-time curve to the last quantifiable concentration (AUClast), with the effectiveness criteria set at a T/R ratio of greater than or equal to 0.77 and a corresponding lower bound for the 90% CI set at 0.71. The upper bound of the 90% CI for safety was defined by the minimum safe plasma concentration (Cmax) in the study used to establish a margin of safety for firocoxib oral paste. Based upon that margin of safety, product safety was defined as a T/R of less than or equal to 1.53, with a corresponding upper bound for the 90% CI of 1.71.

The relative bioavailability study was a randomized, two-period, two sequence crossover study in thirty horses. Each horse received a single tablet (57 mg firocoxib) and a single tube of paste (56.7 mg firocoxib). Blood samples were collected at 15 minutes, 45 minutes, 1, 1.5, 2, 3, 4, 6, 8, 12, 24, 32, 48, 72, 96 and 120hours following each treatment. Samples were analyzed by LC-MS/MS for firocoxib concentrations. The results of the relative bioavailability study are summarized in Table 2. The Cmax and AUClast of firocoxib tablets were within the adjusted 90% CI for safety and effectiveness and met the criteria established for successfully demonstration the firocoxib tablets will be safe and effective. Therefore, firocoxib tablets and firocoxib oral paste are acceptable as pharmaceutical alternatives.

There was a substantial difference in the Tmax (time to maximum plasma concentration) between firocoxib oral paste and firocoxib tablets. The Tmax ranged from 0.25-4 hours for firocoxib oral paste and 0.25-12 hours for firocoxib tablets. The difference in the rate and extent of absorption was greatest within the first three hours after administration. The mean terminal elimination half-life of firocoxib oral paste (45.5 hours) was similar to firocoxib tablet (44.49 hours).

Table 2: Relative Bioavailability Results for firocoxib oral paste (reference) and firocoxib tablets (test) (n=30 horses)
Parameter | Units | Reference; Geometric; Mean | Test; Geometric; Mean | Test/Reference | Lower; 90% CI | Upper; 95% CI
Cmax | ng/mL | 78.44 | 58.85 | 0.75 | 67.92 | 82.88
AUClast | hr*ng/mL | 2515.77 | 2336.32 | 0.93 | 86.37 | 99.85

Cmax = maximum observed plasma concentration

AUClast = Area Under the Curve to the last quantifiable time point

CI = Confidence Interval

The major metabolism mechanism of firocoxib in the horse is decyclopropylmethylation followed by glucuronidation of that metabolite. Based upon radiolabel studies done for the firocoxib paste formulation, the majority of firocoxib is eliminated in the urine as the decyclopropylmethylated metabolite. Despite a high degree of plasma protein binding (98%), firocoxib exhibits a large volume of distribution (mean Vd(ss) = 1652 mL/kg). The terminal elimination half-life (T1/2) in plasma averages 30-40 hours after IV, oral paste or tablet dosing. Therefore, drug accumulation occurs with repeated dose administrations and steady state concentrations are achieved beyond 6-8 daily oral doses in the horse.

Mode of Action

Firocoxib Tablets for Horses is a cyclooxygenase-inhibiting (coxib) class, non-narcotic, non-steroidal anti-inflammatory drug (NSAID) with anti-inflammatory, analgesic and antipyretic activity1 in animal models. Based on in vitro horse data, firocoxib is a selective inhibitor of prostaglandin biosynthesis through inhibition of the inducible cyclooxygenase-2-isoenzyme (COX-2)2. Firocoxib selectivity for the constitutive isoenzyme, cyclooxygenase-1 (COX-1) is relatively low. However, the clinical significance of these in vitro selectivity findings has not been established.

Effectiveness:

The effectiveness of firocoxib tablets was established in a relative bioavailability study comparing firocoxib tablets and firocoxib oral paste. Therefore, additional field studies were not performed to support the effectiveness of firocoxib tablets. (See CLINICAL PHARMACOLOGY, Relative Bioavailability Study).

Two hundred fifty-three client-owned horses of various breeds, ranging in age from 2 to 37 years and weighing from 595 to 1638 lbs, were randomly administered firocoxib oral paste or an active control drug in multi-center field studies. Two hundred forty horses were evaluated for effectiveness and 252 horses were evaluated for safety. Horses were assessed for lameness, pain on manipulation, range of motion, joint swelling, and overall clinical improvement in a non-inferiority evaluation of firocoxib oral paste compared to an active control. At study’s end, 84.4% of horses treated with firocoxib oral paste were judged improved on veterinarians’ clinical assessment, and 73.8% were also rated improved by owners. Horses treated with firocoxib oral paste showed improvement in veterinarian-assessed lameness, pain on manipulation, range of motion, and joint swelling that was comparable to the active control.

Animal Safety:

The safety of firocoxib tablets was supported by a relative bioavailability study comparing firocoxib tablets and firocoxib oral paste (see CLINICAL PHARMACOLOGY, Relative Bioavailability Study), pharmacovigilance information, and target animal safety data for existing firocoxib containing products in horses. No additional target animal safety studies were conducted with firocoxib tablets.

In a target animal safety study conducted to support the approval of firocoxib oral paste, firocoxib was administered orally to healthy adult horses (two male castrates and four females per group) at 0, 0.1, 0.3 and 0.5 mg firocoxib/kg body weight (1, 3 and 5X the recommended dose) for 30 days. Administration of firocoxib at 0.3 and 0.5 mg/kg body weight was associated with an increased incidence of oral ulcers as compared to the control group, but no oral ulcers were noted with 0.1 mg/kg. There were no other drug-related adverse findings in this study.

In another target animal safety study, firocoxib was administered orally to healthy adult horses (four males or male castrates and four females per group) at 0, 0.1, 0.3 and 0.5 mg firocoxib/kg body weight (1, 3 and 5X the recommended dose) for 42 days. Administration of firocoxib at 0.1, 0.3 and 0.5 mg/kg body weight was associated with delayed healing of pre-existing oral (lip, tongue, gingival) ulcers.

In addition, the incidence of oral ulcers was higher in all treated groups as compared to the control group. Clinical chemistry and coagulation abnormalities were seen in several horses in the 0.5 mg/kg (5X) group. One 5X male horse developed a mildly elevated BUN and creatinine over the course of the study, prolonged buccal mucosal bleeding time (BMBT), and a dilated pelvis of the right kidney. Another 5X male had a similar mild increase in creatinine during the study but did not have any gross abnormal findings. One female in the 5X group had a prolonged BMBT, bilateral tubulointerstitial nephropathy and bilateral papillary necrosis.

Tubulointerstitial nephropathy occurred in one 3X female, two 3X male horses, and the 5X female horse discussed above with the prolonged BMBT. Papillary necrosis was present in one 1X male horse and the 5X female horse discussed above. Despite the gross and microscopic renal lesions, all of the horses were clinically healthy and had normal hematology, clinical chemistry and urinalysis values.

In another target animal safety study, firocoxib was administered orally to healthy adult horses (three females, two male castrates and one male per group) at 0, 0.25 mg/kg, 0.75 mg/kg and 1.25 mg/kg (2.5, 7.5 and 12.5X the recommended dose of 0.1 mg/kg) for 92 days. An additional group of three females, two male castrates and one male per group, was dosed at 1.25 mg/kg for 92 days but was monitored until Days 147-149. There were treatment-related adverse events in all treated groups. These consisted of ulcers of the lips, gingiva and tongue and erosions of the skin of the mandible and head. Gross and microscopic lesions of the kidneys consistent with tubulointerstitial nephropathy were seen in all treated groups. Papillary necrosis was seen in the 2.5X and 12.5X groups. In addition, several 12.5X horses had elevated liver enzymes (GGT, SDH, AST and ALT). One 2.5X horse had increased urine GGT and urine protein levels which was due to renal hemorrhage and nephropathy. Gastric ulcers of the margo plicatus and glandular area were more prevalent in the 2.5X and 7.5X groups, but not seen in the 12.5X group. The group of horses that were monitored until Days 147-149 showed partial to full recovery from oral and skin ulcers, but no recovery from tubulointerstitial nephropathy.

In a target animal safety study conducted to assess the safety of firocoxib injection followed by firocoxib oral paste in the horse, thirty-two clinically healthy adult horses received firocoxib injection intravenously once daily for five days at doses of either 0 mg/kg (control group); 0.09 mg/kg (1X); 0.27 mg/kg (3X); or 0.45 mg/kg (5X the recommended dose). This was followed by once daily oral administration of firocoxib oral paste for nine days at doses of either 0 mg/kg (control group); 0.1 mg/kg (1X); 0.3 mg/kg (3X); or 0.5 mg/kg (5X the recommended dose). This sequence (five days of firocoxib injection followed by nine days firocoxib oral paste, for a total of 14 days) was repeated three times for a total treatment duration of 42 days (3X the recommended treatment duration of 14 days). Two male 5X horses demonstrated a white focus in the renal cortex which correlated with tubulointerstitial nephropathy microscopically. The presence of tubulointerstitial nephropathy was considered treatment-related. One horse from the control group and two horses from the 5X group had injection site swellings during treatment. Injection site changes characterized by inflammatory cell influx and rarely tissue necrosis were seen in all study groups including the control group. There was a dose-dependent increase in the incidence of oral ulcers and erosions. Elevated hepatic enzymes (GGT or AST) were noted in all study groups at one or more time points. One male 5X horse with an elevated GGT value on Day 42 was noted to have tubulointerstitial nephropathy at the time of necropsy. For all horses, these hepatic enzyme elevations generally returned to the reference range by the next time point.

Storage Information:

Store at room temperature, between 20-25º C (68-77º F), excursions permitted between 15-40º C (59-104º F).

How supplied:

Firocoxib Tablets for Horses is available as round, beige to tan, half-scored tablets, containing 57 mg firocoxib. Firocoxib Tablets for Horses are supplied in 60 count bottles.

REFERENCES

^1McCann ME, Rickes EL, Hora DF, Cunningham PK et al. In vitro effects and in vivo efficacy of a novel cyclooxygenase-2 inhibitor in cats with lipopolysaccharide-induced pyrexia. Am J Vet Res. 2005 Jul;66 (7): 1278-84.
^2McCann ME, Anderson DR, Brideau C et al. In vitro activity and in vivo efficacy of a novel COX-2 inhibitor in the horse. Proceedings of the Academy of Veterinary Internal Medicine. 2002. Abstract 114, p.789.

Approved by FDA under ANADA # 200-726

Manufactured by:

Pegasus Laboratories, Inc.
Employee-Owned
Pensacola, FL 32514

Rev. 05-2022

Sē●Qual™ and PRN ™ are trademarks of Pegasus Laboratories, Inc.

Information for Horse Owners

Firocoxib Tablets for Horses are administered once daily for up to 14 days for the control of pain and inflammation associated with osteoarthritis in horses.

This summary contains important information about Firocoxib Tablets for Horses. You should read this information before you start giving your horse Firocoxib Tablets for Horses and review it each time your prescription is refilled. This sheet is provided only as a summary and does not take the place of instructions from your veterinarian. Talk to your veterinarian if you need clarification, have questions, or you want to know more about Firocoxib Tablets for Horses.

What is Firocoxib Tablets for Horses?

Firocoxib Tablets for Horses is a veterinary prescription non-steroidal anti-inflammatory drug (NSAID) of the coxib class used to control pain and inflammation associated with osteoarthritis in horses. Osteoarthritis (OA) is a painful condition caused by progressive "wear and tear" of cartilage and other parts of the joints that may result in the following changes or signs in your horse:
• Limping or lameness.
• Decreased activity or exercise (reluctance to stand, walk, trot or run, or difficulty performing these activities).
• Stiffness or decreased movement of joints.

How to give Firocoxib Tablets for Horses to your horse.

Firocoxib Tablets for Horses should be given according to your veterinarian's instructions. Do not change the way you give Firocoxib Tablets for Horses to your horse without first speaking with your veterinarian. Do not exceed 14 days of treatment.

Firocoxib Tablets for Horses may be given with or without food.

What kind of results can I expect when my horse is on Firocoxib Tablets for Horses for OA?

While Firocoxib Tablets for Horses are not a cure for osteoarthritis, it can control the pain and inflammation associated with OA and can improve your horse's mobility.

Which horses should not receive Firocoxib Tablets for Horses?

Your horse should not be given Firocoxib Tablets for Horses if he/she:
• Has an allergic reaction to firocoxib, the active ingredient in Sē●Qual Firocoxib Tablets for Horses.
• Has previously had an allergic reaction (such as hives, facial or lower limb swelling, or red or itchy skin) to aspirin or other NSAIDs.
• Is presently taking aspirin, phenylbutazone, flunixin meglumine, diclofenac, ketoprofen, or other NSAIDs or corticosteroids.
• The safety of Sē●Qual Firocoxib Tablets for Horses has not been determined in horses less than one year of age or in breeding horses, pregnant or lactating mares.

Firocoxib Tablets for Horses should only be given orally to horses.

• Firocoxib Tablets for Horses is not for use in horses intended for human food consumption.
• People should not take Firocoxib Tablets for Horses. Keep Firocoxib Tablets for Horses and all medications out of the reach of children. Consult a physician in case of accidental ingestion by humans.
• Store Firocoxib Tablets for Horses out of reach of dogs and other pets in a secured location in order to prevent accidental ingestion or overdose.

What to tell/ask your veterinarian before giving Sē●Qual Firocoxib Tablets for Horses.

Talk to your veterinarian about:
• The signs of OA you have observed in your horse, such as limping or stiffness.
• If any tests, such as X-rays, will be done before Firocoxib Tablets for Horses is prescribed.
• How often your horse may need to be examined by your veterinarian.
• The risks and benefits of using Firocoxib Tablets for Horses.

Tell your veterinarian if your horse has ever had the following medical problems:

• Any side effects from taking Sē●Qual Firocoxib Tablets for Horses or other NSAIDs, such as aspirin or phenylbutazone.
• Any kidney disease.
• Any liver disease.
• Any gastrointestinal ulcer.

Tell your veterinarian about:

• Other medical problems or allergies that your horse has now or has had in the past.
• All medicines that you are giving or plan to give to your horse, including those you can get without a prescription and any dietary supplements.

Tell your veterinarian if you plan to breed your horse, or if your mare is pregnant or nursing a foal.

What are the possible side effects that may occur in my horse during Firocoxib Tablets for Horses therapy?

Firocoxib Tablets for Horses, like other NSAIDS, may cause some side effects. Serious side effects associated with NSAID therapy in horses can occur with or without warning. The most common side effects associated with Firocoxib Tablets for Horses therapy involve the tongue, lips and skin of the mouth and face (erosions and ulcers of the mucosa and skin) and the kidney. Gastrointestinal, kidney and liver problems have also been reported with other NSAIDs. Look for the following side effects that may indicate your horse is having a problem with Firocoxib Tablets for Horses or may have another medical problem:
• Sores or ulcers on the tongue and inside of mouth.
• Sores, scabs, redness, or rubbing of the facial skin, particularly around the mouth.
• Change in eating or drinking habits (frequency or amount consumed).
• Change in urination habits (frequency or color).
• Yellowing of gums, skin, or whites of the eyes (jaundice).
• Unexpected weight loss.
• Change in behavior (such as increased or decreased activity level).

It is important to stop therapy and contact your veterinarian if you think your horse has a medical problem or side effect while taking Firocoxib Tablets for Horses. If you have additional questions about possible side effects, talk with your veterinarian or call 1-800-874-9764.

Can Firocoxib Tablets for Horses be given with other medications?

Firocoxib Tablets for Horses should not be given with other NSAIDs (for example, aspirin, phenylbutazone, diclofenac, ketoprofen or flunixin) or systemic corticosteroids (for example, prednisone, cortisone, dexamethasone, or triamcinolone).

Tell your veterinarian about all medications that you have given your horse in the past, and any medications you are planning to give with Firocoxib Tablets for Horses. This should include other medicines that you can get without a prescription or any dietary supplements. Your veterinarian may want to check that all of your horse's medicines can be given together.

What do I do in case my horse receives more than the prescribed amount of Firocoxib Tablets for Horses?
• Consult your veterinarian if your horse receives more than the prescribed amount of Firocoxib Tablets for Horses.

What else should I know about Firocoxib Tablets for Horses?

• This sheet provides a summary of information about Firocoxib Tablets for Horses and general information about NSAIDs. If you have any questions or concerns about Firocoxib Tablets for Horses or osteoarthritis pain, talk with your veterinarian.

• As with all prescribed medicines, Firocoxib Tablets for Horses should only be given to the horse for which it is prescribed. It should be given to your horse only for the condition for which it is prescribed, at the labeled dose and duration.

• It is important to periodically discuss your horse's response to Firocoxib Tablets for Horses. Your veterinarian will determine if your horse is responding as expected and if your horse should continue receiving Firocoxib Tablets for Horses.

Rev. 05-2022